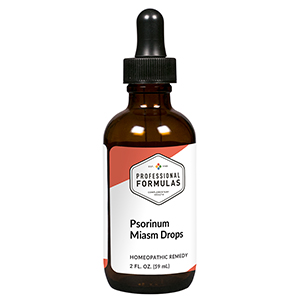 DRUG LABEL: Psorinum Miasm Drops
NDC: 63083-2054 | Form: LIQUID
Manufacturer: Professional Complementary Health Formulas
Category: homeopathic | Type: HUMAN OTC DRUG LABEL
Date: 20190815

ACTIVE INGREDIENTS: ARSENIC TRIOXIDE 30 [hp_X]/59 mL; BARIUM CARBONATE 30 [hp_X]/59 mL; OYSTER SHELL CALCIUM CARBONATE, CRUDE 30 [hp_X]/59 mL; GRAPHITE 30 [hp_X]/59 mL; CALCIUM SULFIDE 30 [hp_X]/59 mL; IODINE 30 [hp_X]/59 mL; MERCURIUS SOLUBILIS 30 [hp_X]/59 mL; SODIUM CHLORIDE 30 [hp_X]/59 mL; PHOSPHORUS 30 [hp_X]/59 mL; SILICON DIOXIDE 30 [hp_X]/59 mL; SULFUR 30 [hp_X]/59 mL; SCABIES LESION LYSATE (HUMAN) 30 [hp_X]/59 mL
INACTIVE INGREDIENTS: ALCOHOL; WATER

C54

ACTIVE INGREDIENTS

Arsenicum album 30X
Baryta carbonica 30X
Calcarea carbonica 30X
Graphites 30X
Hepar sulphuris calcareum 30X
Iodium 30X
Mercurius solubilis 30X
Natrum muriaticum 30X
Phosphorus 30X
Silicea 30X
Sulphur 30X
Psorinum 30X, 60X

QUESTIONS

Professional Formulas

PO Box 2034 Lake Oswego, OR 97035

INDICATIONS

For the temporary relief of dry, itchy, or irritated skin, constipation, flatulence, runny nose, or watery or itchy eyes consistent with classical psorinum miasm.*

PURPOSE

*Claims based on traditional homeopathic practice, not accepted medical evidence. Not FDA evaluated.

WARNINGS

In case of overdose, get medical help or contact a poison control center right away.

Keep out of the reach of children.

PREGNANCY OR BREAST FEEDING

If pregnant or breastfeeding, ask a healthcare professional before use.

DIRECTIONS

Place drops under tongue 30 minutes before/after meals. Adults and children 12 years and over: Take 10 drops up to 3 times per day. Consult a physician for use in children under 12 years of age.

OTHER INFORMATION

Tamper resistant. If seal is broken, do not use. After opening, close container tightly and store at room temperature away from heat.

INACTIVE INGREDIENTS

20% ethanol, purified water.

LABEL

Est 1985

Professional Formulas

Complementary Health

Psorinum Miasm Drops

Homeopathic Remedy

2 FL. OZ. (59 mL)